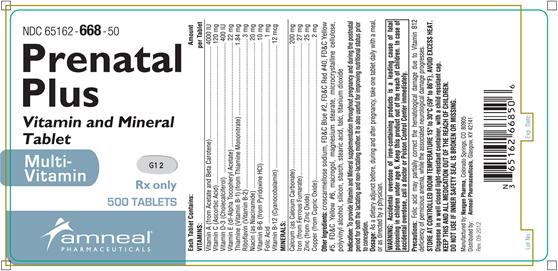 DRUG LABEL: PRENATAL PLUS
NDC: 65162-668 | Form: TABLET, FILM COATED
Manufacturer: Amneal Pharmaceuticals LLC
Category: prescription | Type: HUMAN PRESCRIPTION DRUG LABEL
Date: 20220329

ACTIVE INGREDIENTS: VITAMIN A ACETATE 3080 [iU]/1 1; BETA CAROTENE 920 [iU]/1 1; ASCORBIC ACID 120 mg/1 1; CHOLECALCIFEROL 400 [iU]/1 1; .ALPHA.-TOCOPHEROL ACETATE, DL- 22 mg/1 1; THIAMINE MONONITRATE 1.84 mg/1 1; RIBOFLAVIN 3 mg/1 1; NIACINAMIDE 20 mg/1 1; PYRIDOXINE HYDROCHLORIDE 10 mg/1 1; FOLIC ACID 1 mg/1 1; CYANOCOBALAMIN 12 ug/1 1; CALCIUM CARBONATE 200 mg/1 1; FERROUS FUMARATE 27 mg/1 1; ZINC OXIDE 25 mg/1 1; CUPRIC OXIDE 2 mg/1 1
INACTIVE INGREDIENTS: ASCORBYL PALMITATE; BUTYLATED HYDROXYTOLUENE; CROSCARMELLOSE SODIUM; CALCIUM PHOSPHATE, DIBASIC, DIHYDRATE; .ALPHA.-TOCOPHEROL, DL-; FD&C RED NO. 40; FD&C YELLOW NO. 5; FD&C YELLOW NO. 6; GELATIN; HYPROMELLOSES; MAGNESIUM STEARATE; MALTODEXTRIN; CELLULOSE, MICROCRYSTALLINE; POLYETHYLENE GLYCOL, UNSPECIFIED; PROPYLENE GLYCOL; SILICON DIOXIDE; SODIUM ASCORBATE; SODIUM BENZOATE; SORBIC ACID; STARCH, CORN; STEARIC ACID; SUCROSE; SUNFLOWER OIL; TITANIUM DIOXIDE; TRIACETIN

Prenatal Plus
Vitamin and Mineral Tablet
Multi-Vitamin
Rx Only

DESCRIPTION

Each Tablet Contains:

VITAMINS: Amount per Tablet

Vitamin A (from Acetate and Beta Carotene) ............................. 4000 IU

Vitamin C (Ascorbic Acid) ........................................................... 120 mg

Vitamin D-3 (Cholecalciferol) ....................................................... 400 IU

Vitamin E (dl- Alpha Tocopheryl Acetate) ...................................... 22 mg

Thiamine (Vitamin B-1) (from Thiamine Mononitrate) ................. 1.84 mg

Riboflavin (Vitamin B-2) .................................................................. 3 mg

Niacin (as Niacinamide) ................................................................ 20 mg

Vitamin B-6 (Pyridoxine HCl) ......................................................... 10 mg

Folic Acid ......................................................................................... 1 mg

Vitamin B-12 (Cyanocobalamin) ................................................... 12 mcg

MINERALS: Amount per Tablet

Calcium (as Calcium Carbonate) ................................................. 200 mg

Iron (from Ferrous Fumarate) ........................................................ 27 mg

Zinc (from Zinc Oxide) ................................................................... 25 mg

Copper (from Cupric Oxide) ........................................................... 2 mg

Other ingredients: croscarmellose sodium, FD&C Blue #2, FD&C Red #40, FD&C Yellow # 5, FD&C Yellow # 6, macrogol, magnesium stearate, microcrystalline cellulose, polyvinyl alcohol, silicon, starch, stearic acid, talc, titanium dioxide

INDICATIONS AND USAGE

To provide Vitamin and Mineral supplementation throughout pregnancy and during the postnatal period for both the lactating and non-lactating mother. It is also useful for improving nutritional status prior to conception.

WARNINGS

WARNING: Accidental overdose of iron-containing products is a leading cause of fatal poisoning in children under age 6. Keep this product out of the reach of children. In case of accidental overdose, call a doctor or Poison Control Center immediately.

PRECAUTIONS

Folic acid may partially correct the hematological damage due to Vitamin B12 deficiency of pernicious anemia, while the associated neurological damage progesses.

DOSAGE AND ADMINISTRATION

As a dietary adjunct before, during and after pregnancy, take one tablet daily with a meal, or as directed by a physician.

HOW SUPPLIED

Bottles of 100: NDC 65162-668-10

Bottles of 500: NDC 65162-668-50

Storage

STORE AT CONTROLLED ROOM TEMPERATURE 15º to 30ºC (59º to 86ºF), AVOID EXCESS HEAT.

Dispense in a well closed light-resistant container, with a child resistant cap.
KEEP THIS AND ALL MEDICATION OUR OF THE REACH OF CHILDREN.
DO NOT USE IF INNER SAFETY SEAL IS BROKEN OR MISSING.

Manufactured by:
Nexgen Pharma
Colorado Springs, CO 80905

Distributed by:
Amneal Pharmaceuticals
Glasgow, KY 42141

Rev. 09-2012